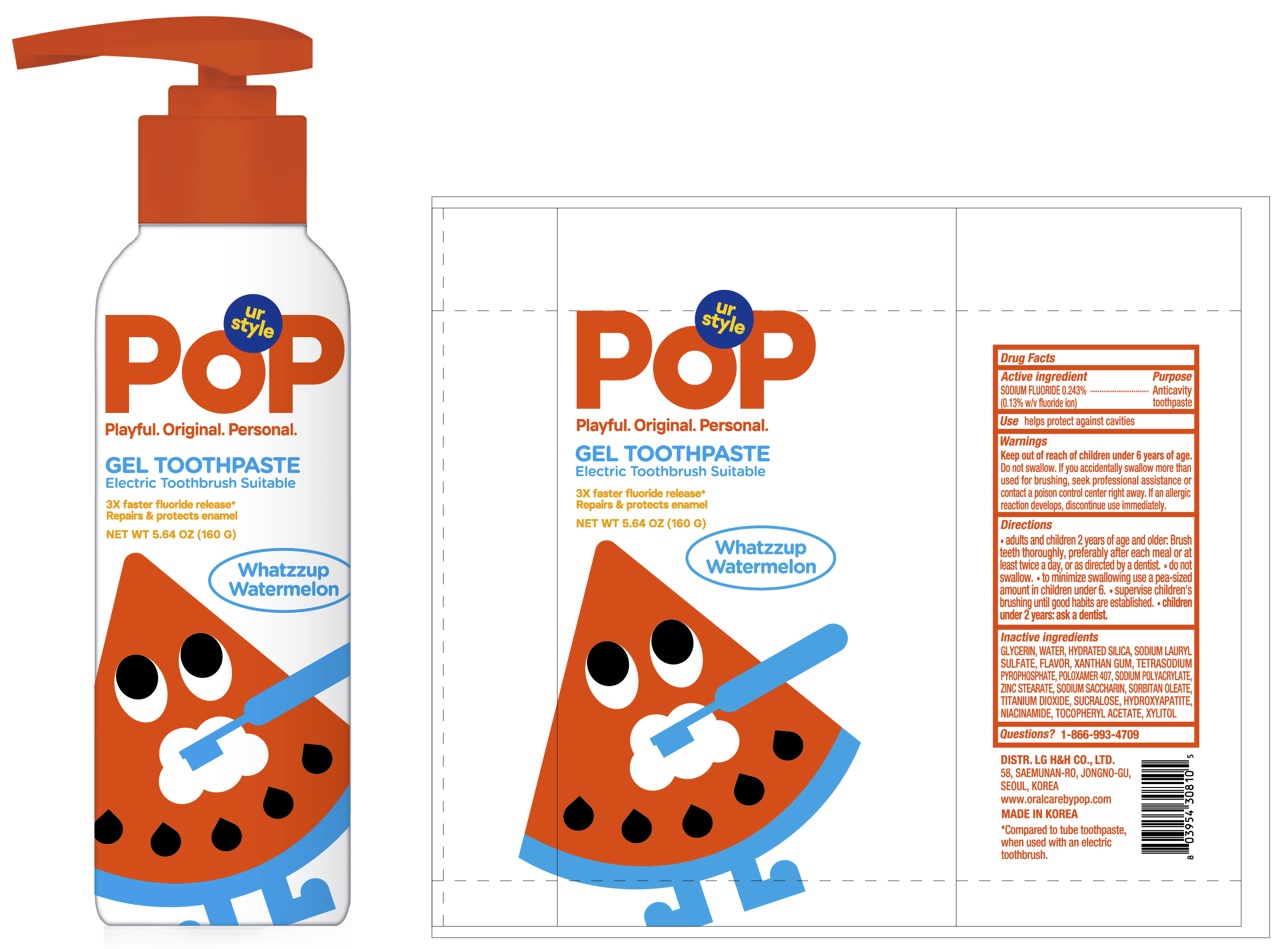 DRUG LABEL: POP Gel Whatzzup Watermelon
NDC: 53208-582 | Form: PASTE, DENTIFRICE
Manufacturer: LG H&H Co., Ltd.
Category: otc | Type: HUMAN OTC DRUG LABEL
Date: 20250101

ACTIVE INGREDIENTS: SODIUM FLUORIDE 1.3 mg/1 g
INACTIVE INGREDIENTS: SORBITAN MONOOLEATE; TRIBASIC CALCIUM PHOSPHATE; NIACINAMIDE; .ALPHA.-TOCOPHEROL ACETATE, DL-; WATER; ZINC STEARATE; GLYCERIN; SODIUM PYROPHOSPHATE; SODIUM LAURYL SULFATE; XANTHAN GUM; SACCHARIN SODIUM; SUCRALOSE; TITANIUM DIOXIDE; XYLITOL; HYDRATED SILICA; SODIUM POLYACRYLATE (8000 MW); POLOXAMER 407

53208-582-60 POP Gel Whatzzup Watermelon Toothpaste 160g

Drug Facts

Active Ingredient

SODIUM FLUORIDE 0.243% (0.13% w/v fluoride ion)

Purpose

Anticavity toopaste

Use

helps protect against cavities

Warnings

Keep out of reach of children under 6 years of age.Do not swallow. If you accidentally swallow more than used for brushing, seek professional assistance or contact a poison control center right away. If an allergic reaction develops, discontinue use immediately.

Directions

- adults and children 2 years of age and and older: Brush teeth thoroughly, preferably after each meal or at least twice a day, or as directed by a dentist.
- do not swallow.
- to minimize swallowing use a pea-sized amount in children under 6.
- supervise children's brushing until good habits are established.
- children under 2 years: ask a dentist.

Inactive Ingredients

GLYCERIN, WATER, HYDRATED SILICA, SODIUM LAURYL SULFATE, FLAVOR, XANTHAN GUM, TETRASODIUM PYROPHOSPHATE, POLOXAMER 407, SODIUM POLYACRYLATE, ZINC STEARATE, SODIUM SACCHARIN, SORBITAN OLEATE, TITANIUM DIOXIDE, SUCRALOSE, HYDROXYAPATITE, NIACINAMIDE, TOCOPHERYL ACETATE, XYLITOL

Questions?

1-866-993-4709

Principal Display Panel - 160 g Tube Carton

POP
Playful. Original. Personal.
GEL TOOTHPASTE
Electric Toothbrush Suitable

3X faster fluoride release*
Repairs & protects enamel

NET WT. 5.64 OZ (160 G)
Whatzzup Watermelon
DISTR. LG H&H CO., LTD.

58, SAEMUNAN-RO, JONGNO-GU,
SEOUL, KOREA
www.oralcarebypop.com
MADE IN KOREA
*Compared to tube toothpaste,
when used with an electric
toothbrush.